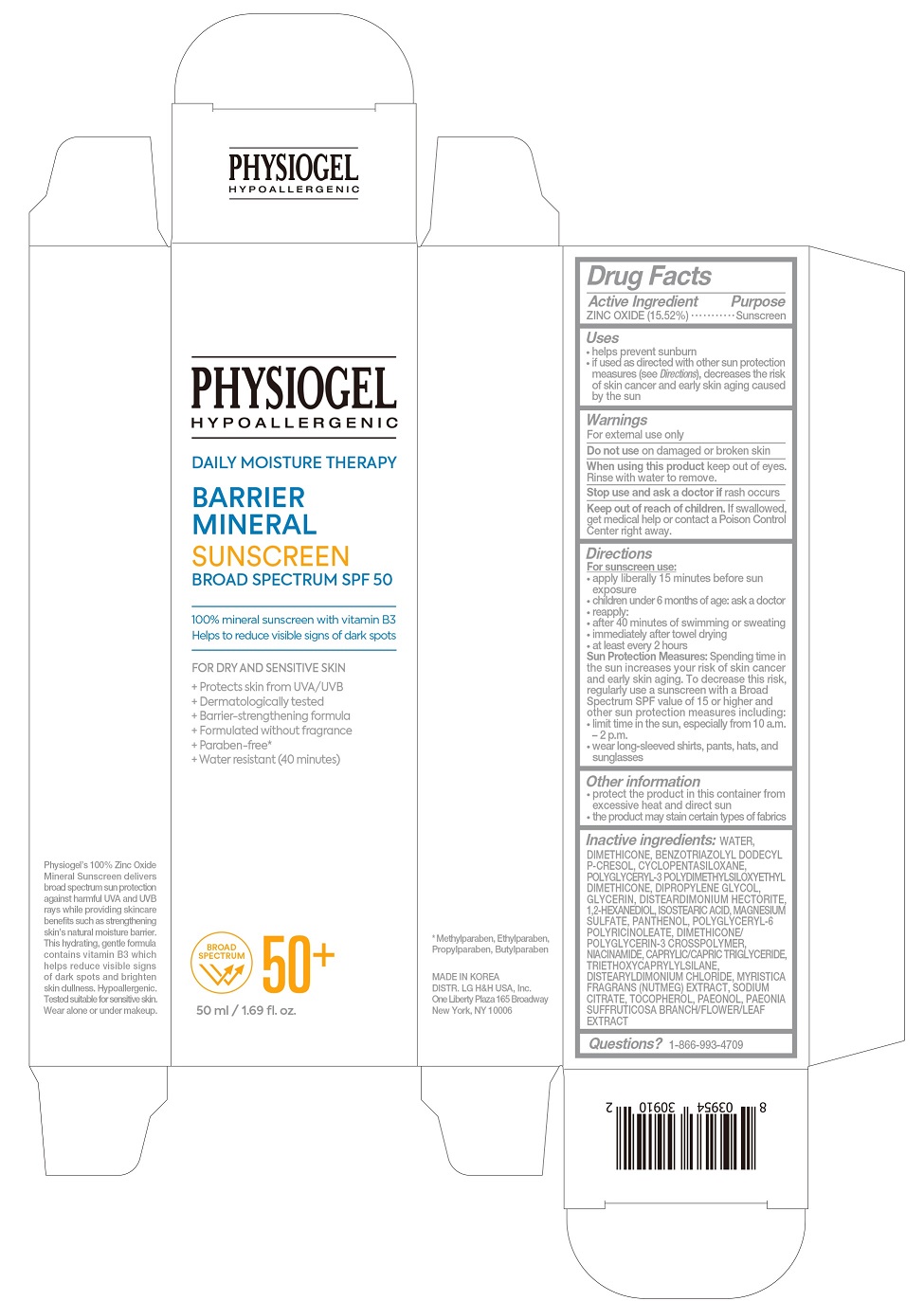 DRUG LABEL: PHYSIOGEL Daily Moisture Therapy Barrier Mineral Sunscreen Broad Spectrum SPF 50
NDC: 72330-251 | Form: CREAM
Manufacturer: fmg Co.Ltd
Category: otc | Type: HUMAN OTC DRUG LABEL
Date: 20240320

ACTIVE INGREDIENTS: ZINC OXIDE 15.52 g/50 mL
INACTIVE INGREDIENTS: WATER

PHYSIOGEL Daily Moisture Therapy Barrier Mineral Sunscreen Broad Spectrum SPF 50

Active Ingredient

ZINC OXIDE (15.52%)

Purpose

Sunscreen

Uses

- helps prevent sunburn
- if used as directed with other sun protection measures (see Directions), decreases the risk of skin cancer and early skin aging caused by the sun

Warnings

For external use only

- Do not use on damaged or broken skin

- When using this product keep out of eyes. Rinse with water to remove.

- Stop use and ask a doctor if rash occurs

- Keep out of reach of children. If swallowed, get medical help or contact a Poison Control Center right away.

Directions

For sunscreen use:

- apply liberally 15 minutes before sun exposure
- children under 6 months of age: ask a doctor
- reapply
- - after 40 minutes of swimming or sweating
- - immediately after towel drying
- - at least every 2 hours

Sun Protection Measures:Spending time in the sun increases your risk of skin cancer and early skin aging. To decrease this risk, regularly use a sunscreen with a Broad Spectrum SPF value of 15 or higher and other sun protection measures including:

- limit time in the sun, especially from 10 a.m.-2 p.m.
- wear long-sleeved shirts, pants, hats, and sunglasses

Other information

- protect the product in this container from excessive heat and direct sun
- the product may stain certain types of fabrics

Inactive ingredients:

WATER

Questions?

1-866-993-4709

* Methylparaben, Ethylparaben,
Propylparaben, Butylparaben

MADE IN KOREA
DISTR. LG H&H USA, Inc.
One Liberty Plaza 165 Broadway

Physiogel's 100% Zinc Oxide Mineral Sunscreen deliveres broad spectrum sun protection against harmful UVA and UVB rays while providing skincare benefits such as strengthening skin's natural moisture barrier. This hydrating, gentle formula contains vitamin B3 which helps reduce visible signs of dark spots and brighten skin dullness. Hypoallergenic. Tested suitable for sensitive skin. Wear alone or under makeup.

PRINCIPAL DISPLAY PANEL

PHYSIOGEL

HYPOALLERGENIC

DAILY MOISTURE THERAPY

BARRIER
MINERAL
SUNSCREEN
BROAD SPECTRUM SPF 50

----------------------------------------------------------
100% mineral sunscreen with vitamin B3
Helps to reduce visible signs of dark spots
----------------------------------------------------------

FOR DRY AND SENSITIVE SKIN
+ Protects skin from UVA/UVB
+ Dermatologically tested
+ Barrier-strengthening formula
+ Paraben-free*
+ Water resistant (40 minutes)

BROAD
SPECTRUM 50+

50 ml / 1.69 fl.oz.